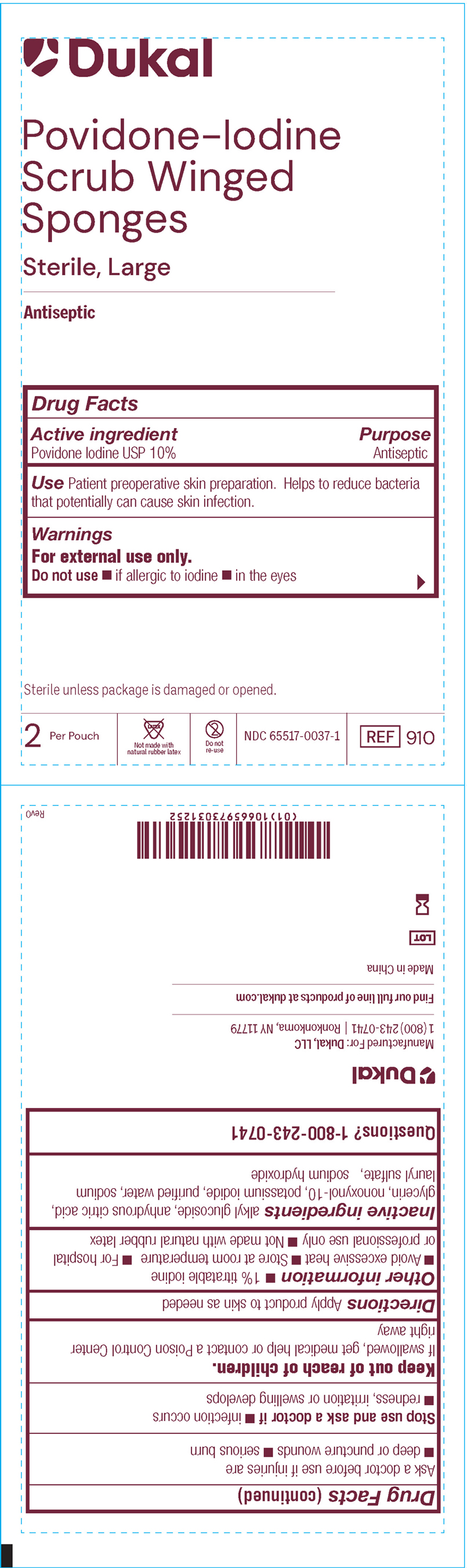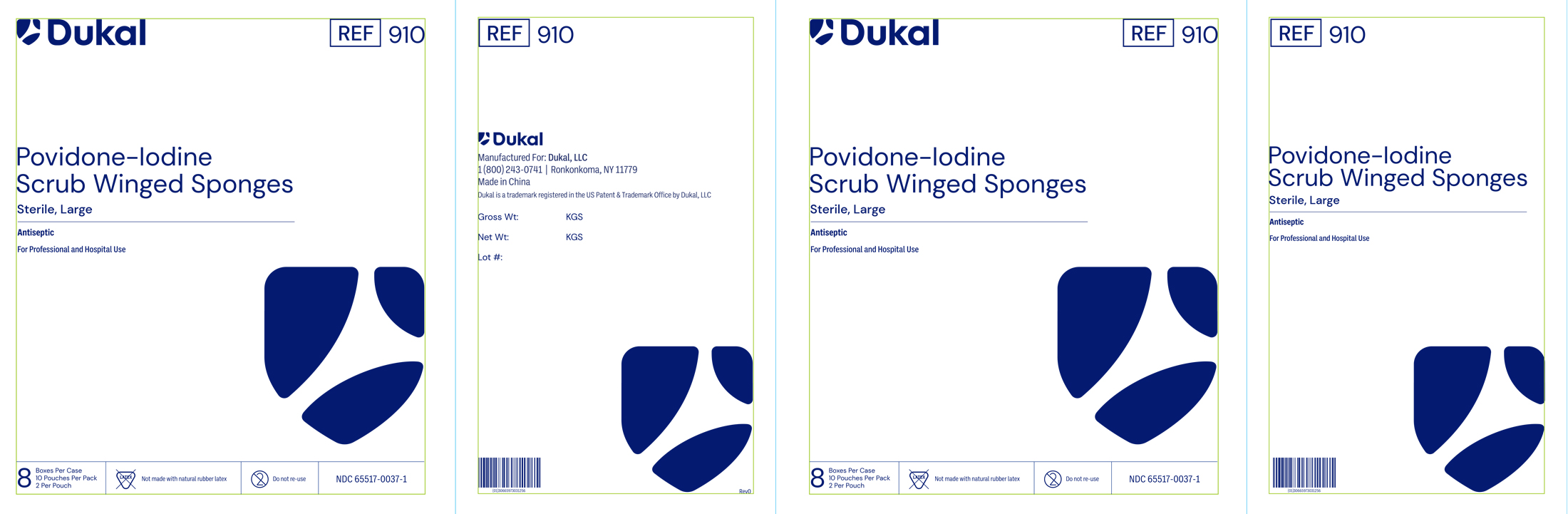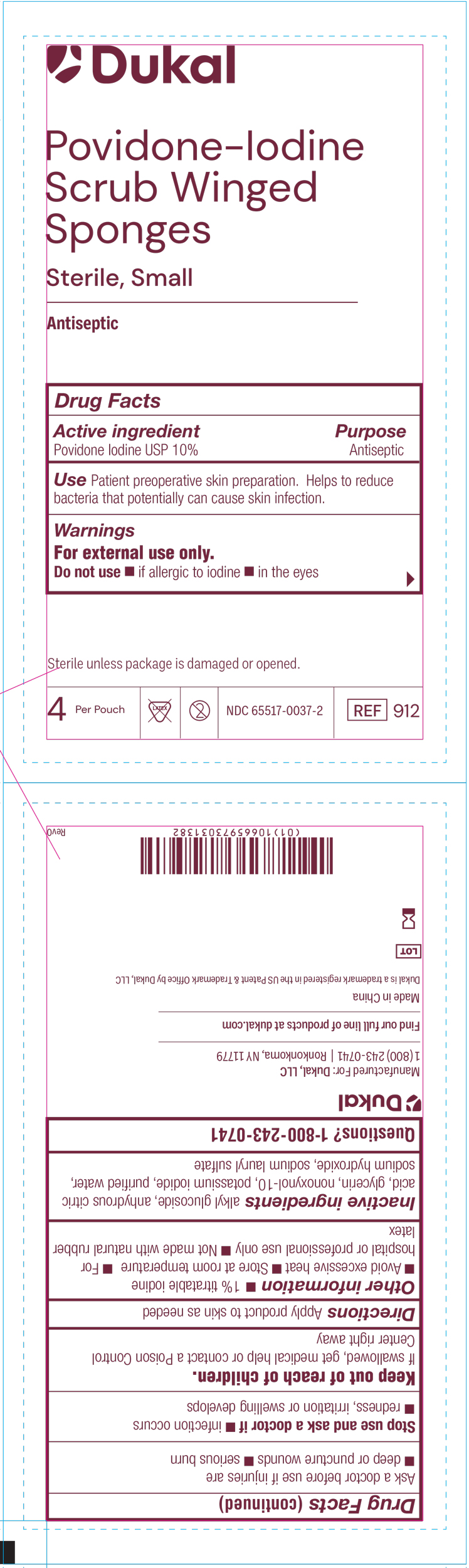 DRUG LABEL: Dukal Povidone-Iodine Scrub Winged Sponges
NDC: 65517-0037 | Form: SPONGE
Manufacturer: Dukal LLC
Category: otc | Type: HUMAN OTC DRUG LABEL
Date: 20251119

ACTIVE INGREDIENTS: POVIDONE-IODINE 1.1 g/100 mL
INACTIVE INGREDIENTS: ANHYDROUS CITRIC ACID; POTASSIUM IODIDE; GLYCERIN; NONOXYNOL-10; WATER; C12-20 ALKYL GLUCOSIDE; SODIUM LAURYL SULFATE; SODIUM HYDROXIDE

65517-0037

Active Ingredient

Povidone-Iodine USP 10%

Purpose

Antiseptic

Use

Patient preoperative skin preparation. Helps to reduc bacteria that potentially can cause skin infection.

Warnings:

For external use only.

- Do not apply to persons allergic to iodine. Do not use in the eyes.

- Ask a doctor before use if injuries are deep wounds, puncture wounds, serious burns.

Stop use and ask doctor if infection occurs, redness, irritation or swelling develops.

- Keep out of reach of children
- If swallowed or gets in eyes, get medical help or contact Poison Control Center right away.

Directions

Apply product to skin as needed.

Other Information:

1% titratable iodine, Avoid excessive heat, Store at room temperature, For hospital or professional use only, Not made with natural rubber latex

Inactive Ingredients:

Alkyl Glucoside, Anhydrous Citric Acid, Glycerin, Nonoxynol-10, Potassium Iodide, Purified Water, Sodium Lauryl Sulfate, Sodium Hydroxide

PACKAGE LABEL

Dukal™

Povidone-Iodine

Scrub Winged

Sponges

Sterile, Large

Antispetic

Drug Facts

Active ingredient Purpose

Povidone Iodine USP 10% Antiseptic

Use Patient preoperative skin preparation. Helps to reduce bacteria

that potentially can cause skin infection.

Warnings

For external use only.

Do no use if allergic to iodine, in the eyes

Sterile unless package is damagedor opened

2 Per Pouch Not Made with Natural Rubber Latex Do not re-use NDC-66517-0037-1 REF 910

PACKAGE LABEL

Dukal REF 910

Povidone-Iodine

Scrub Winged Sponges

Sterile, Large
Antiseptic

For Professional and Hospital Use

8 Boxes Per Case

10 Pouches Per Pack

2 Per Pouch

Not Made with Natural Rubber Latex Do not re-use NDC 65517-0037-1

PACKAGE LABEL

Dukal™

Povidone-Iodine

Scrub Winged

Sponges

Sterile, Small

Antispetic

Drug Facts

Active ingredient Purpose

Povidone Iodine USP 10% Antiseptic

Use Patient preoperative skin preparation. Helps to reduce bacteria

that potentially can cause skin infection.

Warnings

For external use only.

Do no use if allergic to iodine, in the eyes

Sterile unless package is damagedor opened

4 Per Pouch Not Made with Natural Rubber Latex Do not re-use NDC-66517-0037-2 REF 912